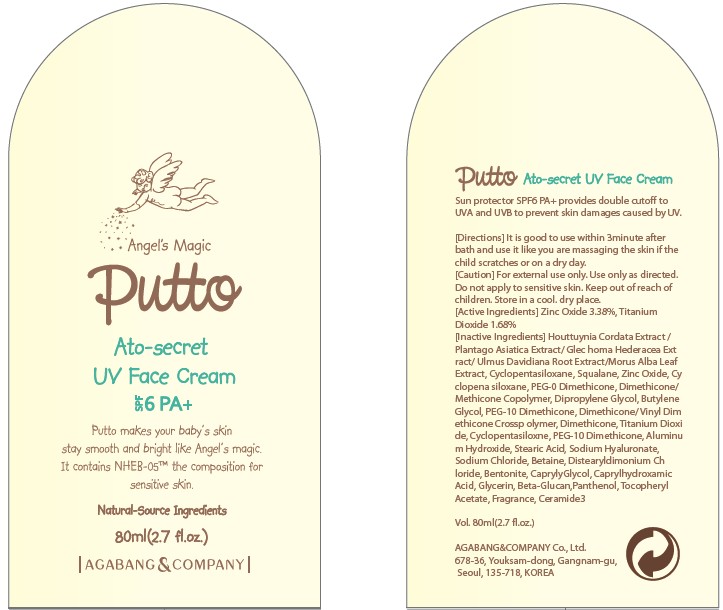 DRUG LABEL: PUTTO ATO SECRET UV FACE
NDC: 75885-010 | Form: CREAM
Manufacturer: AGABANG & COMPANY
Category: otc | Type: HUMAN OTC DRUG LABEL
Date: 20110217

ACTIVE INGREDIENTS: ZINC OXIDE 2.70 mL/80 mL; TITANIUM DIOXIDE 1.34 mL/80 mL
INACTIVE INGREDIENTS: PLANTAGO MAJOR; GLECHOMA HEDERACEA; SQUALANE; DIPROPYLENE GLYCOL; BUTYLENE GLYCOL

Drug Facts

Active Ingredients: ZINC OXIDE, TITANIUM DIOXIDE

Inactive Ingredients:

HOUTTUYNIA CORDATA EXTRACT, PLANTAGO ASIATICA EXTRACT, GLECHOMA HEDERACEA FLOWER/LEAF/STEM EXTRACT, MORUS ALBA LEAF EXTRACT, ULMUS DAVIDIANA ROOT EXTRACT, CYCLOPENTASILOXANE, SQUALANE, PEG-10 DIMETHICONE, METHICONE COPOLYMER, DIPROPYLENE GLYCOL, BUTYLENE GLYCOL, VINYL DIMETHICONE CROSSPOLYMER, DIMETHICONE, ALUMINUM HYDROXIDE, STEARIC ACID, SODIUM CHLORIDE, BETAINE, DISTEARYLDIMONIUM CHLORIDE, BENTONITE, CAPRYLYL GLYCOL, CAPRYLHYDROXAMIC ACID, GLYCERIN, BETA-GLUCAN, PANTHENOL, TOCOPHERYL ACETATE, FRAGRANCE, CERAMIDE 3

Directions:
It is good to use within 3minute after bath and use it like you are massaging the skin if the child scratches or on a dry day.
Caution:
For external use only.
Use only as directed.
Do not apply to sensitive skin.
Keep out of reach of children.
Store in a cool. dry place.